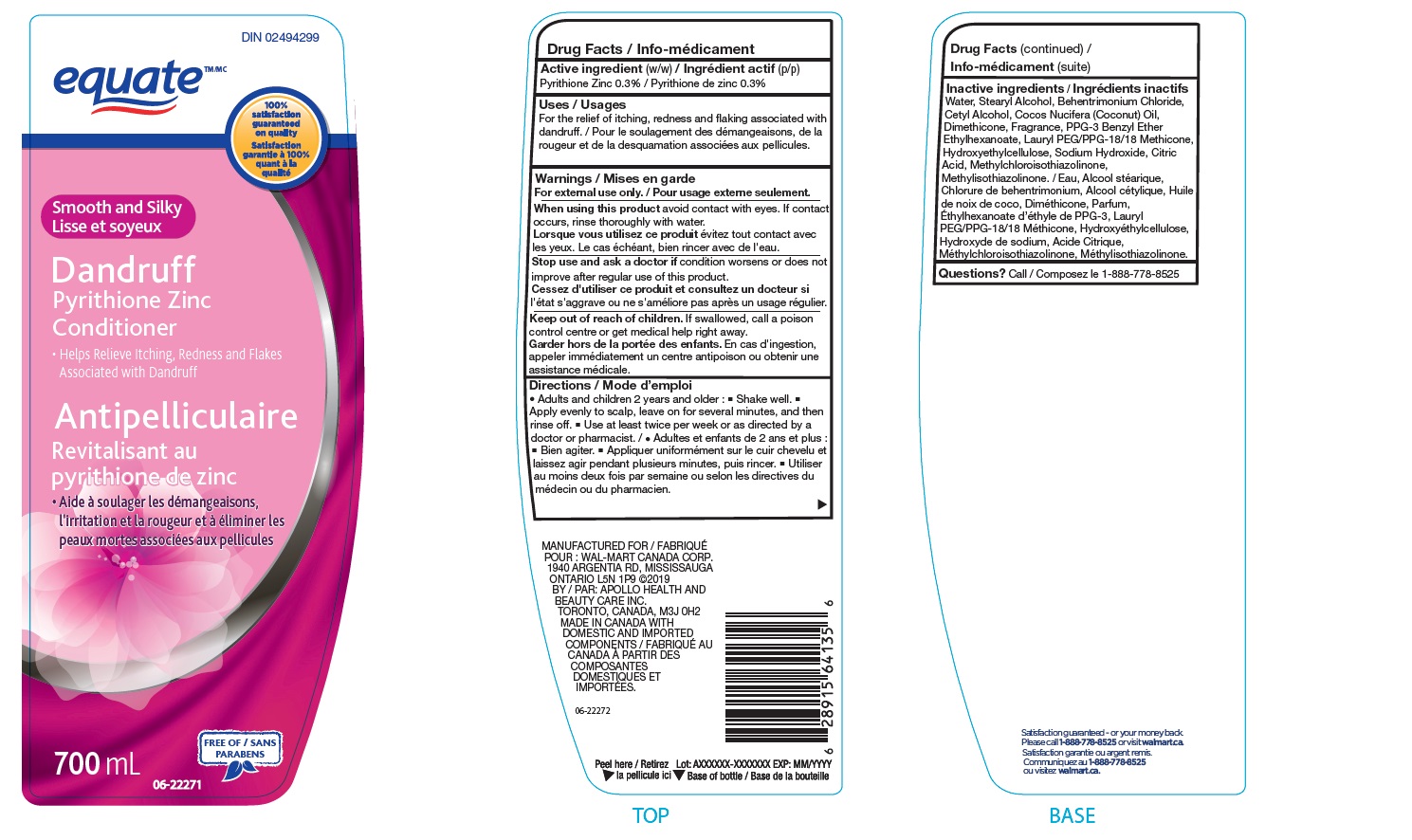 DRUG LABEL: Walmart
NDC: 79903-899 | Form: LOTION/SHAMPOO
Manufacturer: Wal-Mart Stores, Inc
Category: otc | Type: HUMAN OTC DRUG LABEL
Date: 20250104

ACTIVE INGREDIENTS: PYRITHIONE ZINC 300 mg/100 mL
INACTIVE INGREDIENTS: BEHENTRIMONIUM CHLORIDE; FRAGRANCE CLEAN ORC0600327; METHYLCHLOROISOTHIAZOLINONE/METHYLISOTHIAZOLINONE MIXTURE; ANHYDROUS CITRIC ACID; LAURYL PEG/PPG-18/18 METHICONE; CETYL HYDROXYETHYLCELLULOSE (350000 MW); STEARYL ALCOHOL; SODIUM HYDROXIDE; PPG-3 BENZYL ETHER ETHYLHEXANOATE; WATER; CETYL ALCOHOL; COCONUT OIL; DIMETHICONE

NDC- 79903-899, Equate Smooth & Silky

ACTIVE INGREDIENT

Pyrithione Zinc

PURPOSE

For the relief of itching, redness and flaking associated with dandruff

WARNINGS

For External use

WHEN USING

avoid contact with eyes. If contact occurs, rinse thoroughly with water.

Stop use and ask a doctor ifcondition worsens or does not improve after regular use of this product.

Keep out of reach of children. If swallowed, call a poison control centre or get medical help right away.

DOSAGE AND ADMINISTRATION

- Adults and children 2 years and older.
- Shake well.
- Apply evenly to scalp. leave on for several minutes and then rinse off.
- Use at least twice per week or as directed by a doctor or pharmacist.

INACTIVE INGREDIENT

Water, Stearyl Alcohol, Behentrimonium Chloride, Cetyl Alcohol, Cocos Nucifera (Coconut) Oil,
Dimethicone, Fragrance, PPG-3 Benzyl Ether Ethylhexanoate, Lauryl PEG/PPG-18/18 Methicone,
Hydroxyethylcellulose, Sodium Hydroxide, Citric Acid, Methylchloroisothiazolinone,
Methylisothiazolinone.

STORAGE AND HANDLING

Store at room temperature

INDICATIONS AND USAGE

Relieves itching , redness and flakes associated with Dandruff.